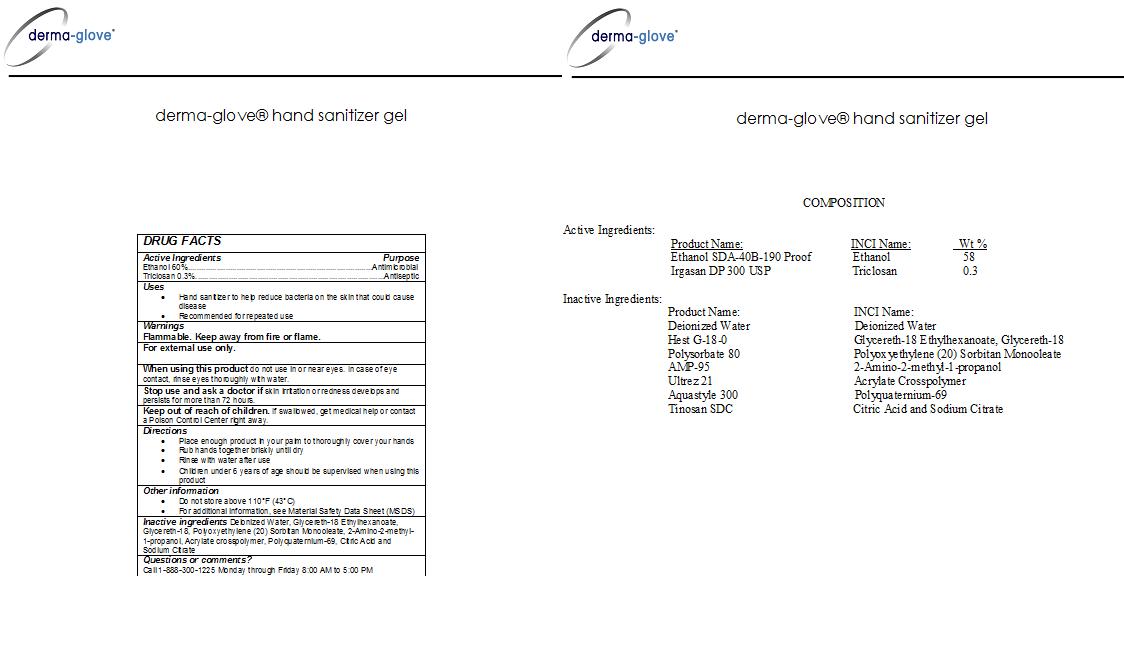 DRUG LABEL: Derma-Glove
NDC: 24673-248 | Form: GEL
Manufacturer: RWM TECHNOLOGIES
Category: otc | Type: HUMAN OTC DRUG LABEL
Date: 20100601

ACTIVE INGREDIENTS: Ethanol 0.58 g/1 g; Triclosan 0.03 g/1 g

DERMA-GLOVE HAND SANITIZER GEL

DESCRIPTION

DERMA-GLOVE(R) no rinse hand sanitizer gel

Active Ingredient

Ethanol 60%..................................................................Antimicrobial

Triclosan 0.3%..............................................................Antiseptic

PURPOSE

Antiseptic/Antimicrobial hand sanitizer gel

INDICATIONS AND USAGE

- Hand sanitizer to help reduce bacteria on the skin that could cause disease
- Recommended for repeated use

Warnings

Flammable. Keep away from fire or flame.

For external use only.

When using this product do not use in or near eyes. In case of eye contact, rinse eyes thoroughly with water.

Stop use and ask a doctor if skin irritation or redness develops and persists for more than 72 hours.

KEEP OUT OF REACH OF CHILDREN

Keep out of the Reach of Children. If swallowed, get medical help or contact a Poison Control Center right away.

Directions:

- Place enough product in your palm to thoroughly cover your hands
- Rub hands together briskly until dry
- Rinse with water after use
- Children under 6 years of age should be supervised when using this product

GENERAL PRECAUTIONS

- Do not store above 110o F (43o C)
- For additional information, see Material Safety Data Sheet (MSDS).

INACTIVE INGREDIENT

Deionized Water, Glycereth-18 Ethylhexanoate, Glycereth-18, Polyoxyethylene (20) Sorbitan Monooleate, 2-Amino-2-methyl-1-propanol, Acrylate crosspolymer, Polyquaternium-69, Citric Acid and Sodium Citrate

Questions or Comments?

Call 1-888-300-1225 Monday through Friday 8:00 AM to 5:00 PM

LABEL